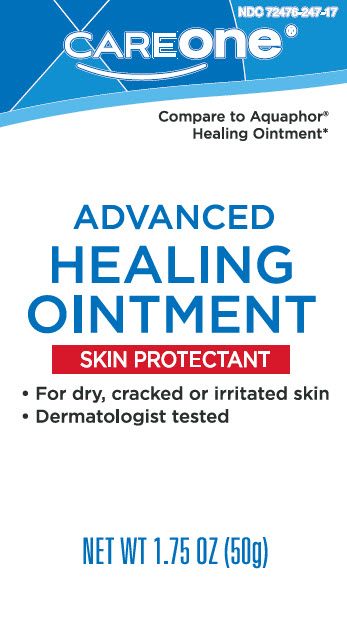 DRUG LABEL: Advanced Healing
NDC: 72476-247 | Form: OINTMENT
Manufacturer: Retail Business Services, LLC
Category: otc | Type: HUMAN OTC DRUG LABEL
Date: 20260206

ACTIVE INGREDIENTS: PETROLATUM 410 mg/1 g
INACTIVE INGREDIENTS: MINERAL OIL; CERESIN; LANOLIN ALCOHOLS; PANTHENOL; GLYCERIN; LEVOMENOL

Care One 247.000/247AA-AC
Healing Ointment for Dry and Cracked Skin

Active ingredient

Petrolatum 41%

Purpose

Skin protectant

Uses

■ temporarily protects minor: ■ cuts ■ scrapes ■ burns
■ temporarily protects and helps relieve chapped or cracked skin and lips
■ helps protect from the drying effects of wind and cold weather

Warnings

For external use only

Do not use on

■ deep or puncture wounds ■ animal bites ■ serious burns

When using this product

■ do not get into eyes

Stop use and ask a doctor if

■ condition worsens
■ symptoms last more than 7 days or clear up and occur again within a few days

Keep out of reach of children.

If swallowed, get medical help or contact a Poison Control Center right away.

Directions

- apply as needed

Inactive ingredients

mineral oil, ceresin, lanolin alcohol, panthenol, glycerin, bisabolol

*This product is not manufactured or distributed by Beiersdorf, Inc., distributor of Aquaphor® Healing Ointment.

DISTRIBUTED BY:

ADUSA DISTRIBUTION, LLC

SALISBURY, NC 28147

For product questions or concerns,

contact us at 1-833-992-3872

Quality guaranteed or your money back.

principal panel display

NDC 72476-247-17

CAREONE

Compare to Aquaphor Healing Ointment*

ADVACNE HEALING OINTMENT

SKIN PROTECTANT

- For dry, cracked or irritated skin
- Dermatologist tested

NET WT 1.75 oz (50g)